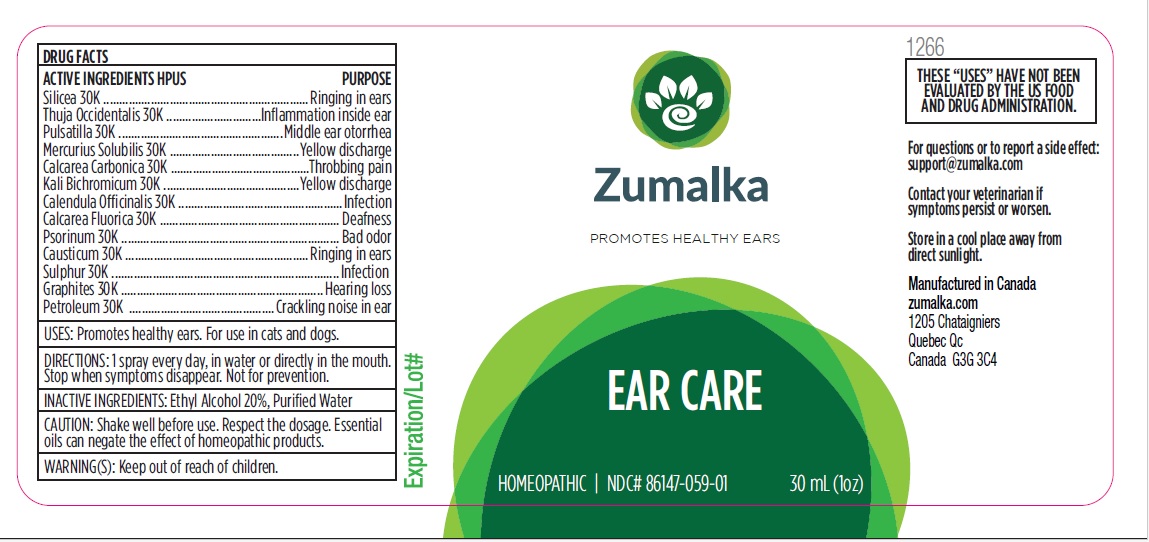 DRUG LABEL: EAR CARE
NDC: 86147-059 | Form: LIQUID
Manufacturer: Groupe Cyrenne Inc.
Category: homeopathic | Type: OTC ANIMAL DRUG LABEL
Date: 20251120

ACTIVE INGREDIENTS: SILICON DIOXIDE 30 [kp_C]/30 mL; THUJA OCCIDENTALIS LEAFY TWIG 30 [kp_C]/30 mL; PULSATILLA VULGARIS WHOLE 30 [kp_C]/30 mL; MERCURIUS SOLUBILIS 30 [kp_C]/30 mL; OYSTER SHELL CALCIUM CARBONATE, CRUDE 30 [kp_C]/30 mL; POTASSIUM DICHROMATE 30 [kp_C]/30 mL; CALENDULA OFFICINALIS FLOWERING TOP 30 [kp_C]/30 mL; CALCIUM FLUORIDE 30 [kp_C]/30 mL; SCABIES LESION LYSATE (HUMAN) 30 [kp_C]/30 mL; CAUSTICUM 30 [kp_C]/30 mL; SULFUR 30 [kp_C]/30 mL; GRAPHITE 30 [kp_C]/30 mL; KEROSENE 30 [kp_C]/30 mL
INACTIVE INGREDIENTS: ALCOHOL; WATER

Active ingredients Purpose

Silicea 30k Ringing in ears

Thuja Occidentalis 30k Inflammation inside ear

Pulsatilla 30k Middle ear otorrhea

Mercurius Solubilis 30k Yellow discharge

Calcarea Carbonica 30k Throbbing pain

Kali Bichromicum 30k Yellow discharge

Calendula Officinalis 30k Infection

Calcarea Fluorica 30k Deafness

Psorinum 30k Bad odor

Causticum 30k Ringing in ears

Sulphur 30k Infection

Graphites 30k Hearing loss

Petroleum 30k Crackling noise in ear

Uses

Promotes healthy ears. For use in cats and dogs.

Warnings

Keep out of reach of children.

Direction

1 spray every day, in water or directly in the mouth. Stop when symptoms disappear. Not for prevention.

Inactive ingredients

Ethyl alcohol 20%, purified water

Cautions

Shake well before use. Respect the dosage. Essential oils can negate the effects of homeopathic products. Store in a cool place away from direct sunlight.